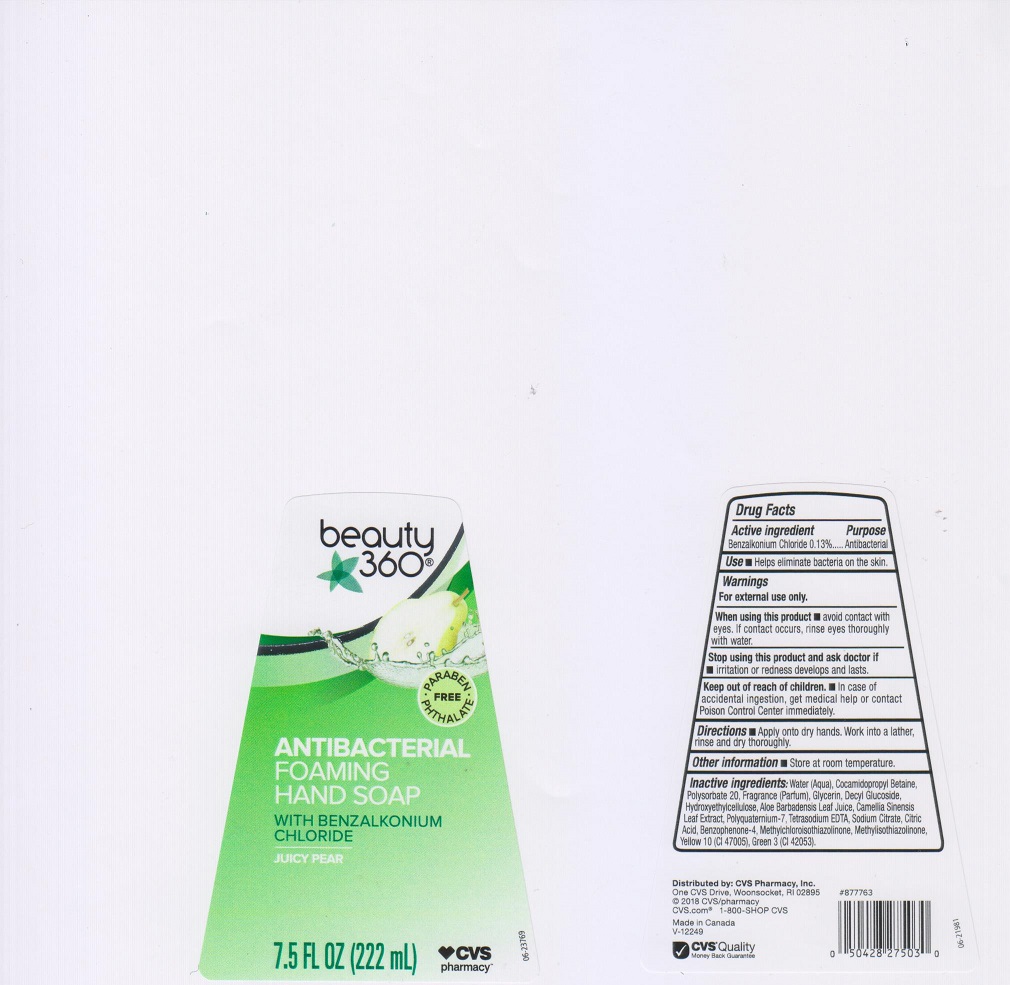 DRUG LABEL: CVS Pharmacy
NDC: 59779-113 | Form: LIQUID
Manufacturer: CVS Pharmacy
Category: otc | Type: HUMAN OTC DRUG LABEL
Date: 20200318

ACTIVE INGREDIENTS: BENZALKONIUM CHLORIDE 1.3 mg/1 mL
INACTIVE INGREDIENTS: WATER; COCAMIDOPROPYL BETAINE; POLYSORBATE 20; GLYCERIN; DECYL GLUCOSIDE; HYPROMELLOSES; ALOE VERA LEAF; GREEN TEA LEAF; POLYQUATERNIUM-7 (70/30 ACRYLAMIDE/DADMAC; 1600000 MW); EDETATE SODIUM; SODIUM CITRATE; CITRIC ACID MONOHYDRATE; SULISOBENZONE; METHYLCHLOROISOTHIAZOLINONE; METHYLISOTHIAZOLINONE; D&C YELLOW NO. 10; FD&C GREEN NO. 3

Drug Facts

Active ingredient

Benzalkonium Chloride 0.13%

Purpose

Antibacterial

Use

- Helps eliminate bacteria on the skin.

Warnings

For external use only.

When using this product

- avoid contact with eyes. If contact occurs, rinse eyes thoroughly with water.

Stop using this product and ask doctor if

- irritation or redness develops and lasts.

Keep out of reach of children.

- In case of accidental ingestion, get medical help or contact a Poison Control Center immediately.

Directions

- Apply onto dry hands. Work into a lather, rinse and dry thoroughly.

Other information

- store at room temperature.

Inactive ingredients

Water (Aqua), Cocamidopropyl Betaine, Polysorbate 20, Fragrance (Parfum), Glycerin, Decyl Glucoside, Hydroxyethylcellulose, Aloe Barbadensis Leaf Juice, Camellia Sinensis Leaf Extract, Polyquaternium-7, Tetrasodium EDTA, Sodium Citrate, Citric Acid, Benzophenone-4, Methylchloroisothiazolinone, Methylisothiazolinone, Yellow 10 (CI 47005), Green 3 (CI 42053).